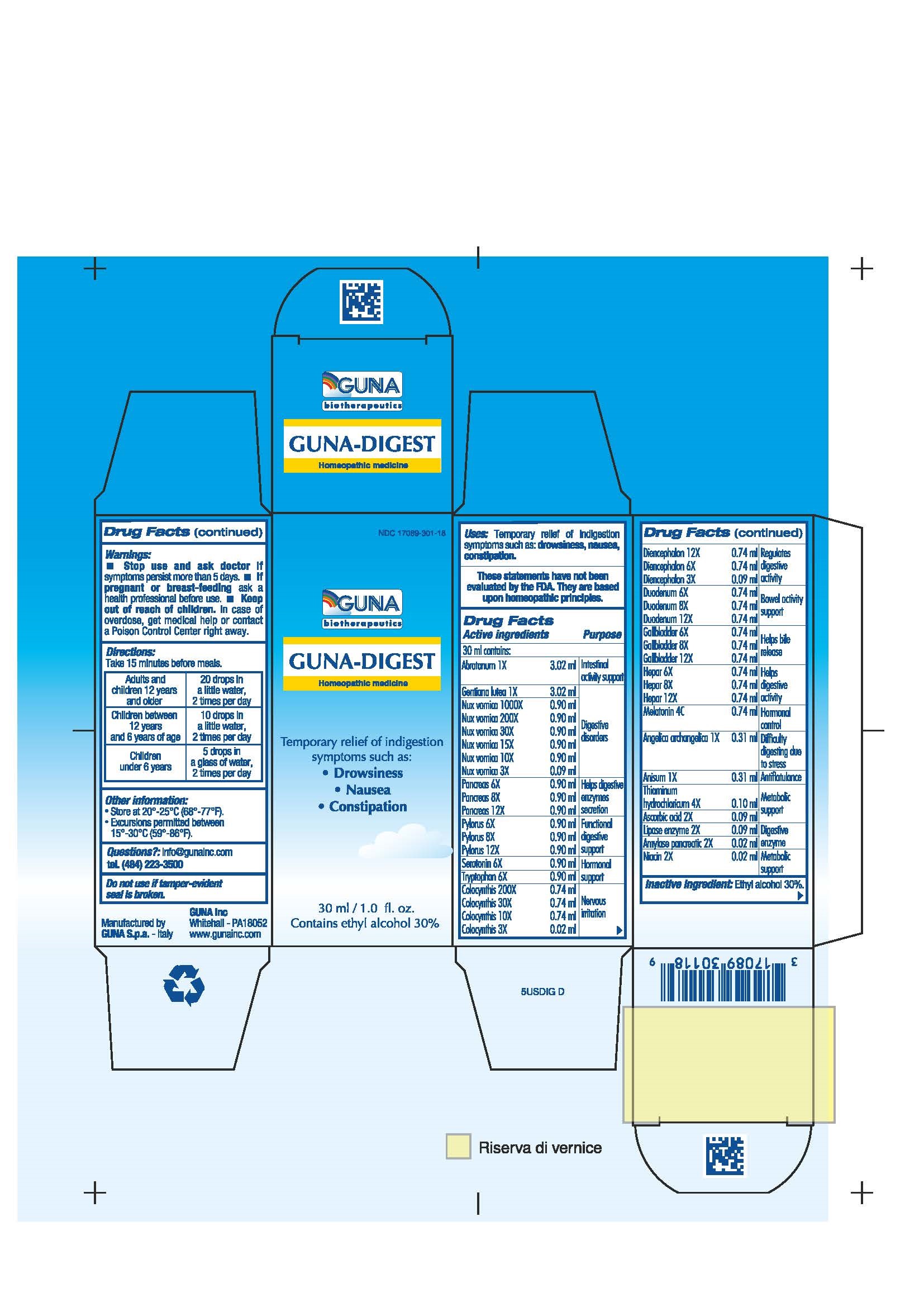 DRUG LABEL: GUNA-DIGEST
NDC: 17089-301 | Form: SOLUTION/ DROPS
Manufacturer: Guna spa
Category: homeopathic | Type: HUMAN OTC DRUG LABEL
Date: 20181222

ACTIVE INGREDIENTS: ARTEMISIA ABROTANUM FLOWERING TOP 1 [hp_X]/30 mL; PANCRELIPASE AMYLASE 2 [hp_X]/30 mL; ANGELICA ARCHANGELICA ROOT 1 [hp_X]/30 mL; ANISUM 1 [hp_X]/30 mL; ASCORBIC ACID 2 [hp_X]/30 mL; CITRULLUS COLOCYNTHIS FRUIT PULP 3 [hp_X]/30 mL; SUS SCROFA DIENCEPHALON 6 [hp_X]/30 mL; SUS SCROFA DUODENUM 8 [hp_X]/30 mL; SUS SCROFA GALLBLADDER 8 [hp_X]/30 mL; GENTIANA LUTEA ROOT 1 [hp_X]/30 mL; PORK LIVER 8 [hp_X]/30 mL; PANCRELIPASE LIPASE 2 [hp_X]/30 mL; MELATONIN 4 [hp_C]/30 mL; NIACIN 2 [hp_X]/30 mL; STRYCHNOS NUX-VOMICA SEED 3 [hp_X]/30 mL; SUS SCROFA PANCREAS 8 [hp_X]/30 mL; SUS SCROFA PYLORUS 8 [hp_X]/30 mL; SEROTONIN 6 [hp_X]/30 mL; THIAMINE HYDROCHLORIDE 4 [hp_X]/30 mL; TRYPTOPHAN 6 [hp_X]/30 mL; TRYPSIN 2 [hp_X]/30 mL
INACTIVE INGREDIENTS: ALCOHOL

GUNA-DIGEST

ACTIVE INGREDIENTS/PURPOSE

ABROTANUM 1X INTESTINAL ACTIVITY SUPPORT
AMYLASE PANCREATIC 2X DIGESTIVE ENZYME
ANGELICA ARCHANGELICA 1X DIFFICULTY DIGESTING DUE TO STRESS
ANISUM 1X ANTIFLATULANCE
ASCORBIC ACID 2X METABOLIC SUPPORT
COLOCYNTHIS 3X 10X 30X 200X NERVOUS IRRITATION
DIENCEPHALON 3X 6X 12X REGULATES DIGESTIVE ACTIVITY
DUODENUM 6X 8X 12X BOWEL ACTIVITY SUPPORT
GALL BLADDER 6X 8X 12X HELPS BILE RELEASE
GENTIANA LUTEA 1X DIGESTIVE DISORDERS
HEPAR 6X 8X 12X HELPS DIGESTIVE ACTIVITY
LIPASE ENZYME 2X DIGESTIVE ENZYME
MELATONIN 4C HORMONAL CONTROL
NIACIN 2X METABOLIC SUPPORT
NUX VOMICA 3X 10X 15X 30X 200X 1000X DIGESTIVE DISORDERS
PANCREAS 6X 8X 12X HELPS DIGESTIVE ENZYMES SECRETION
PYLORUS 6X 8X 12X FUNCTIONAL DIGESTIVE SUPPORT
SEROTONIN 6X HORMONAL SUPPORT
THIAMINUM HYDROCHLORICUM 4X METABOLIC SUPPORT
TRYPSIN 2X DIGESTIVE ENZYME
TRYPTOPHAN 6X HORMONAL SUPPORT

USES

Temporary relief of indigestion symptoms such as:

- Drowsiness
- Nausea
- Constipation

WARNINGS

- Stop use and ask doctor if symptoms persist more than 5 days or worsen.
- I f pregnant or breast-feeding ask a health professional before use.
- Keep out of reach of children. In case of overdose, get medical help or contact a Poison Control Center right away.
- Contains ethyl alcohol 30%

PREGNANCY

If pregnant or breast-feeding ask a doctor before use

WARNINGS

Keep out of reach of children

DIRECTIONS

- Adults and children 12 years and older 20 drops in a little water, 2 times per day
- Children between 12 years and 6 years of age 10 drops in a little water, 2 times per day
- Children under 6 years 5 drops in a glass of water, 2 times per day

QUESTIONS

Questions?: info@gunainc.com, tel. (484) 223-3500

Inactive ingredient: Ethyl alcohol 30%

INDICATIONS AND USAGE

Take 15 minutes before meals.